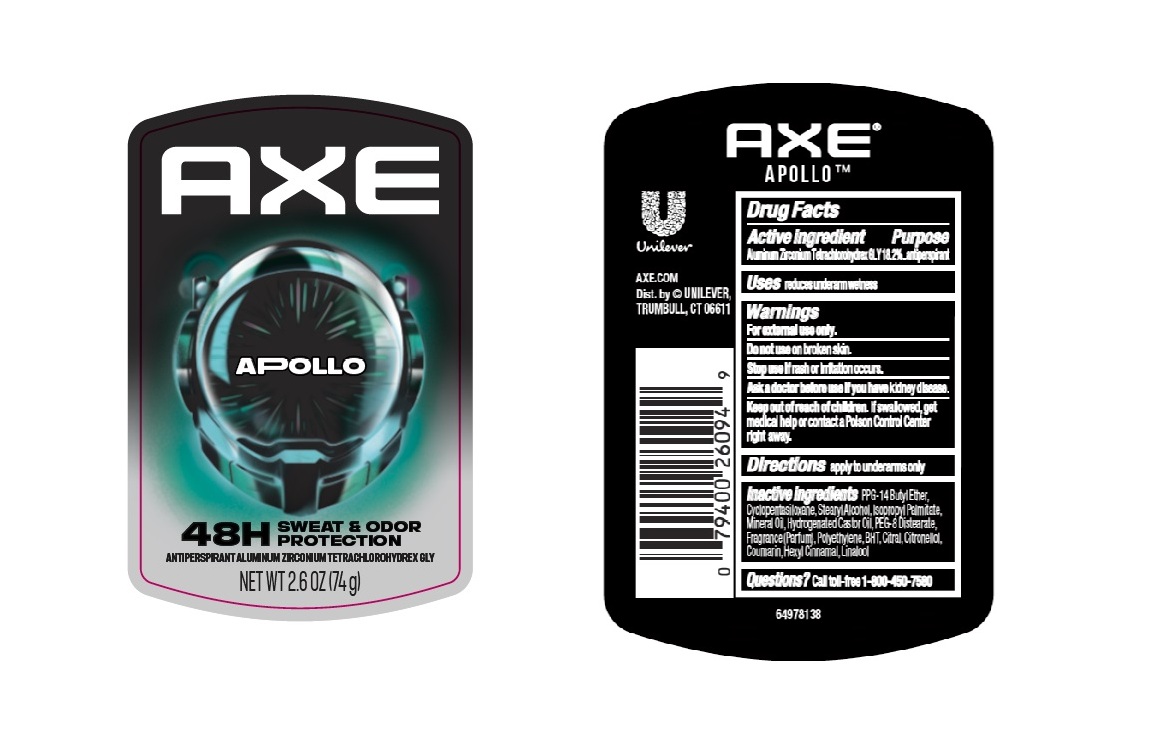 DRUG LABEL: Axe
NDC: 64942-2396 | Form: STICK
Manufacturer: Conopco, Inc. d/b/a Unilever
Category: otc | Type: HUMAN OTC DRUG LABEL
Date: 20251121

ACTIVE INGREDIENTS: ALUMINUM ZIRCONIUM TETRACHLOROHYDREX GLY 18.2 g/100 g
INACTIVE INGREDIENTS: CYCLOPENTASILOXANE; POLYETHYLENE; STEARYL ALCOHOL; BHT; PPG-14 BUTYL ETHER; CITRAL; HYDROGENATED CASTOR OIL; CITRONELLOL; LINALOOL, (+/-)-; MINERAL OIL; ISOPROPYL PALMITATE; PEG-8 DISTEARATE; COUMARIN; HEXYL CINNAMAL

Axe Apollo 48H Sweat and Odor Protection Antiperspirant Deodorant Stick

DESCRIPTION

Axe Apollo 48H Sweat and Odor Protection Antiperspirant Deodorant Stick

ACTIVE INGREDIENT

Aluminum Zirconium Tetrachlorohydrex GLY 18.2%

PURPOSE

Antiperspirant

INDICATIONS AND USAGE

reduces underarm wetness

WARNINGS

For external use only. • Do not use on broken skin. • Stop use if rash or irritation occurs.• Ask a doctor before use if you have kidney disease.

Keep out of reach of children. If swallowed,get medical help or contact a Poison Control Center right away.

DOSAGE AND ADMINISTRATION

apply to underarms only

INACTIVE INGREDIENT

PPG-14 Butyl Ether,Cyclopentasiloxane,Stearyl Alcohol,Isopropyl Palmitate,Mineral Oil,Hydrogenated Castor Oil,PEG-8 Distearate, Fragrance (Parfum),Polyethylene,BHT,Citral,Citronellol,Coumarin,Hexyl Cinnamal,Linalool

QUESTIONS

Call toll-free 1-800-450-7580